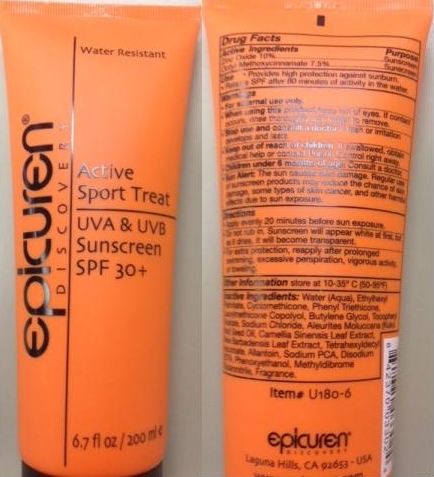 DRUG LABEL: Epicuren Discovery SPF 30
NDC: 59663-130 | Form: LOTION
Manufacturer: Shine & Pretty (USA), Corp.
Category: otc | Type: HUMAN OTC DRUG LABEL
Date: 20130709

ACTIVE INGREDIENTS: OCTINOXATE 75 mg/1 mL; ZINC OXIDE 100 mg/1 mL
INACTIVE INGREDIENTS: VITAMIN A PALMITATE; CHAMOMILE; CUCUMBER; ETHYLHEXYL PALMITATE; CYCLOMETHICONE; BUTYLENE GLYCOL; .ALPHA.-TOCOPHEROL ACETATE; SODIUM CHLORIDE; KUKUI NUT; CAMELLIA OLEIFERA SEED; ALOE VERA LEAF; TETRAHEXYLDECYL ASCORBATE; ALLANTOIN; SODIUM PYRROLIDONE CARBOXYLATE; EDETATE DISODIUM; ETHYLHEXYLGLYCERIN; METHYLISOTHIAZOLINONE

Epicuren Discovery SPF 30

Active Ingredients

Octinoxate, 7.5% (UVB sunscreen), Zinc oxide, 10.0% (UVA/UVB sunscreen)

Warnings

For external use only, not to be swallowed. Avoid contact with eye. Discontinue if signs of irritation or rash appear.

Purpose

For Sun protection for surfaces of skin, face, arm and hand. SPF-15 provides the face and body skin with effective protection against harmful UVA and UVB rays. Use daily over moisture cream to help prevent premature aging and wrinkling due to prolonged exposure to the sun, reapply after swimming or excessive exercise.
Paraben and PABA free.
Fairly water resistant.
Not tested on animals.
Made in the USA specifically for professional dermatology and esthetic practices.

Directions for Use

Home Care: Apply SPF 30 liberally to face and body at least ten minutes before sun exposure or two minutes before applying makeup. Reapply after swimming or excessive perspiration. As part of effective age-fighting program, apply every morning throughout the year. Because SPF 30 is a blend of UV absorbing and reflecting sunscreens, it may be applied over or under moisturizer.
Facial Procedure: SPF 30 is recommended as the finishing product at the end of the facial procedure for any skin type. It may be applied over finishing cream or moisturizer. It should not be rubbed in completely, but left on the skin until it becomes transparent.

Inactive Ingredients

Water, ethylhexyl palmitate, cyclomethicone, laurylmethicone, butylene glycol, tocopheryl acetate, sodium chloride, kukui (aleurites moluccana) seed oil (lipid-rich plant oil), green tea (camellia oleifera) seed extract, aloe vera (aloe barbadensis) leaf extract, tetrahexyldecyl ascorbate (time-released age-fighting vitamin C), allantoin, sodium PCA (hydrating), disodium EDTA, ethylhexylglycerin, methylisothiazolinone, fragrance (synthetic citrus).

Questions?

(805) 388-8581

Keep Out of the reach of children. Use on children under six months of age only with the advice of a physician.

Principal Panel Display

MM1